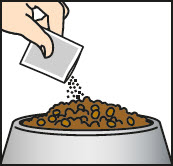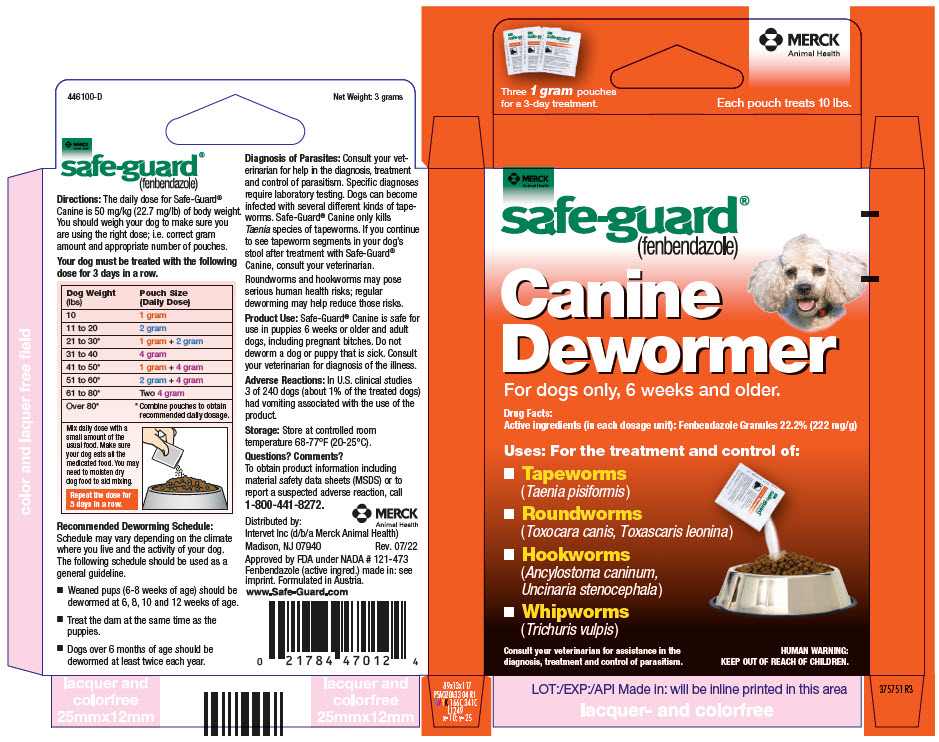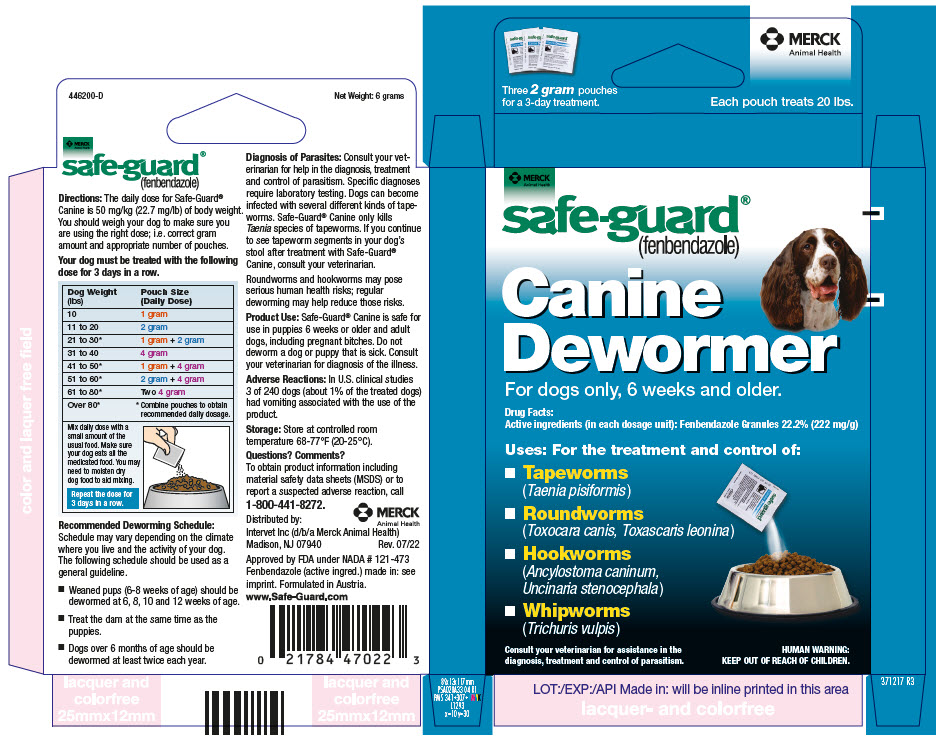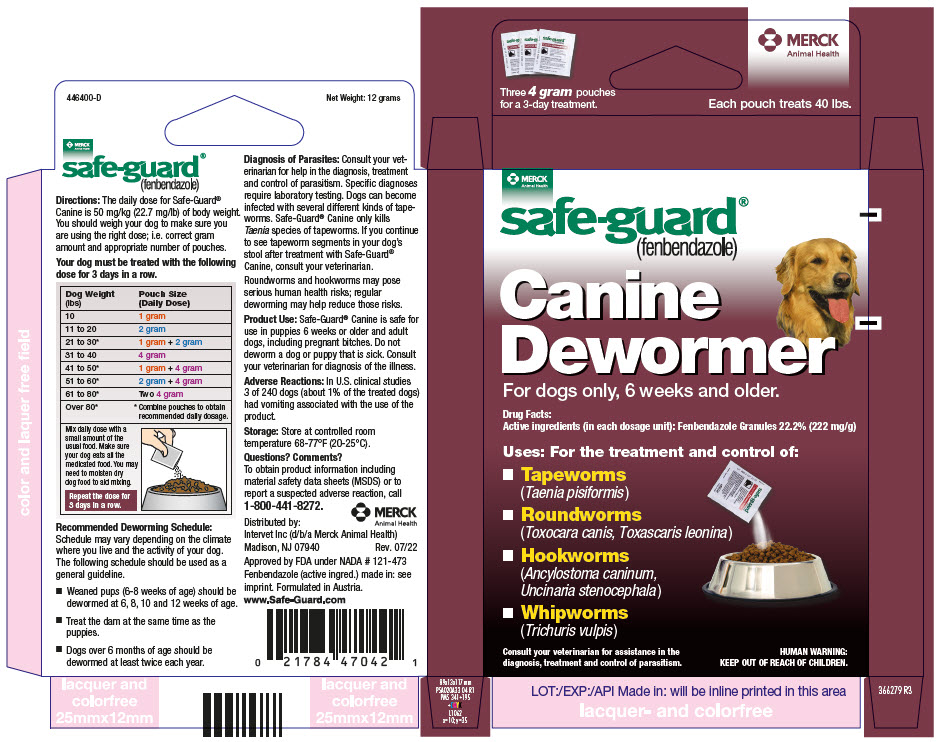 DRUG LABEL: Safe-guard
NDC: 57926-483 | Form: GRANULE
Manufacturer: Merck Sharp & Dohme Corp.
Category: animal | Type: OTC ANIMAL DRUG LABEL
Date: 20241115

ACTIVE INGREDIENTS: FENBENDAZOLE 222 mg/1 g

safe-guard®
(fenbendazole)

DOSAGE AND ADMINISTRATION

Directions: The daily dose for Safe-Guard® Canine is 50 mg/kg (22.7 mg/lb) of body weight. You should weigh your dog to make sure you are using the right dose; i.e. correct gram amount and appropriate number of pouches.

Your dog must be treated with the following dose for 3 days in a row.

Dog Weight (lbs) | Pouch Size (Daily Dose)
10 | 1 gram
11 to 20 | 2 gram
21 to 30 [Combine pouches to obtain recommended daily dosage.] | 1 gram + 2 gram
31 to 40 | 4 gram
41 to 50 | 1 gram + 4 gram
51 to 60 | 2 gram + 4 gram
61 to 80 | Two 4 gram
Over 80
Mix daily dose with a small amount of the usual food. Make sure your dog eats all the medicated food. You may need to moisten dry dog food to aid mixing. Repeat the dose for 3 days in a row.

Recommended Deworming Schedule:

Schedule may vary depending on the climate where you live and the activity of your dog. The following schedule should be used as a general guideline.

- Weaned pups (6-8 weeks of age) should be dewormed at 6, 8, 10 and 12 weeks of age.
- Treat the dam at the same time as the puppies.
- Dogs over 6 months of age should be dewormed at least twice each year.

Diagnosis of Parasites: Consult your veterinarian for help in the diagnosis, treatment and control of parasitism. Specific diagnoses require laboratory testing. Dogs can become infected with several different kinds of tapeworms. Safe-Guard® Canine only kills Taenia species of tapeworms. If you continue to see tapeworm segments in your dog's stool after treatment with Safe-Guard® Canine, consult your veterinarian.

Roundworms and hookworms may pose serious human health risks; regular deworming may help reduce those risks.

INDICATIONS AND USAGE

Product Use: Safe-Guard® Canine is safe for use in puppies 6 weeks or older and adult dogs, including pregnant bitches. Do not deworm a dog or puppy that is sick. Consult your veterinarian for diagnosis of the illness.

ADVERSE REACTIONS

Adverse Reactions: In U.S. clinical studies 3 of 240 dogs (about 1% of the treated dogs) had vomiting associated with the use of the product.

STORAGE AND HANDLING

Storage: Store at controlled room temperature 68-77°F (20-25°C).

Questions? Comments?

To obtain product information including material safety data sheets (MSDS) or to report a suspected adverse reaction, call 1-800-441-8272.

MERCK
Animal Health

Distributed by:
Intervet Inc (d/b/a Merck Animal Health)
Madison, NJ 07940

Rev. 07/22

Approved by FDA under NADA # 121-473

Fenbendazole (active ingred.) made in: see imprint. Formulated in Austria.

www.Safe-Guard.com

PRINCIPAL DISPLAY PANEL - 3 Pouch Carton - 10 lbs

MERCK
Animal Health

safe-guard®
(fenbendazole)

Canine
Dewormer

For dogs only, 6 weeks and older.

Drug Facts:
Active ingredients (in each dosage unit): Fenbendazole Granules 22.2% (222 mg/g)

Uses: For the treatment and control of:

- Tapeworms
  (Taenia pisiformis)
- Roundworms
  (Toxocara canis, Toxascaris leonina)
- Hookworms
  (Ancylostoma caninum,
  Uncinaria stenocephala)
- Whipworms
  (Trichuris vulpis)

Consult your veterinarian for assistance in the
diagnosis, treatment and control of parasitism.

HUMAN WARNING:
KEEP OUT OF REACH OF CHILDREN.

PRINCIPAL DISPLAY PANEL - 3 Pouch Carton - 20 lbs

MERCK
Animal Health

safe-guard®
(fenbendazole)

Canine
Dewormer

For dogs only, 6 weeks and older.

Drug Facts:
Active ingredients (in each dosage unit): Fenbendazole Granules 22.2% (222 mg/g)

Uses: For the treatment and control of:

- Tapeworms
  (Taenia pisiformis)
- Roundworms
  (Toxocara canis, Toxascaris leonina)
- Hookworms
  (Ancylostoma caninum,
  Uncinaria stenocephala)
- Whipworms
  (Trichuris vulpis)

Consult your veterinarian for assistance in the
diagnosis, treatment and control of parasitism.

HUMAN WARNING:
KEEP OUT OF REACH OF CHILDREN.

PRINCIPAL DISPLAY PANEL - 3 Pouch Carton - 40 lbs

MERCK
Animal Health

safe-guard®
(fenbendazole)

Canine
Dewormer

For dogs only, 6 weeks and older.

Drug Facts:
Active ingredients (in each dosage unit): Fenbendazole Granules 22.2% (222 mg/g)

Uses: For the treatment and control of:

- Tapeworms
  (Taenia pisiformis)
- Roundworms
  (Toxocara canis, Toxascaris leonina)
- Hookworms
  (Ancylostoma caninum,
  Uncinaria stenocephala)
- Whipworms
  (Trichuris vulpis)

Consult your veterinarian for assistance in the
diagnosis, treatment and control of parasitism.

HUMAN WARNING:
KEEP OUT OF REACH OF CHILDREN.